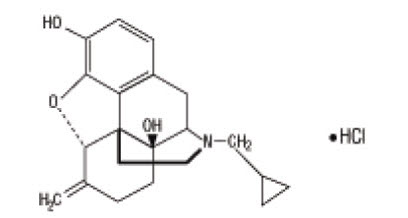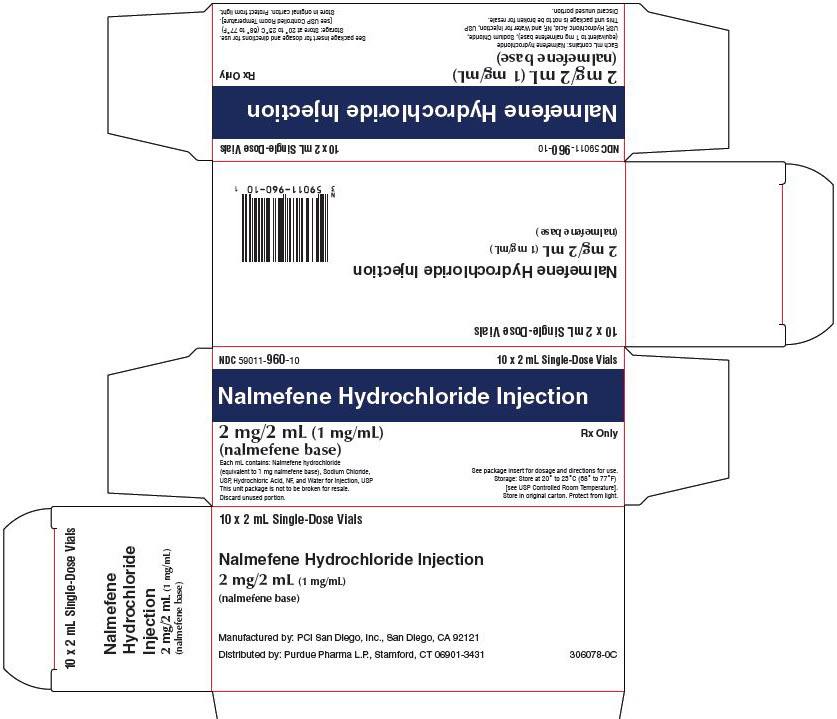 DRUG LABEL: NALMEFENE HYDROCHLORIDE
NDC: 59011-960 | Form: INJECTION, SOLUTION
Manufacturer: Purdue Pharma L.P.
Category: prescription | Type: HUMAN PRESCRIPTION DRUG LABEL
Date: 20251117

ACTIVE INGREDIENTS: NALMEFENE HYDROCHLORIDE 1 mg/1 mL
INACTIVE INGREDIENTS: SODIUM CHLORIDE 9 mg/1 mL; HYDROCHLORIC ACID; WATER

Nalmefene Hydrochloride Injection

Rx only

DESCRIPTION

Nalmefene hydrochloride injection, an opioid antagonist, is a 6-methylene analogue of naltrexone. The chemical structure is shown below:

Molecular Formula: C21H25NO3∙HCl

Molecular Weight: 375.9, CAS # 58895-64-0

Chemical Name: 17-(Cyclopropylmethyl)-4,5a-epoxy-6-methylenemorphinan-3,14-diol, hydrochloride salt.

Nalmefene hydrochloride is a white to off-white crystalline powder which is freely soluble in water up to 130 mg/mL and slightly soluble in chloroform up to 0.13 mg/mL, with a pKa of 7.6.

Nalmefene hydrochloride injection is available as a sterile solution for intravenous, intramuscular, and subcutaneous administration in concentration of 1 mg of nalmefene free base per mL. The 1 mg/mL concentration contains 1.108 mg of nalmefene hydrochloride per mL, 9.0 mg of sodium chloride per mL, and the pH is adjusted to 3.9 with hydrochloric acid.

Concentration and dosage of nalmefene hydrochloride injection are expressed as the free base equivalent of nalmefene.

CLINICAL PHARMACOLOGY

Pharmacodynamics

Nalmefene hydrochloride injection prevents or reverses the effects of opioids, including respiratory depression, sedation, and hypotension. Pharmacodynamic studies have shown that nalmefene hydrochloride injection has a longer duration of action than naloxone at fully reversing doses. Nalmefene hydrochloride injection has no opioid agonist activity.

Nalmefene hydrochloride injection is not known to produce respiratory depression, psychotomimetic effects, or pupillary constriction. No pharmacological activity was observed when nalmefene hydrochloride injection was administered in the absence of opioid agonists.

Nalmefene hydrochloride injection has not been shown to produce tolerance, physical dependence, or abuse potential.

Nalmefene hydrochloride injection can produce acute withdrawal symptoms in individuals who are opioid dependent.

Pharmacokinetics

Nalmefene exhibited dose proportional pharmacokinetics following intravenous administration of 0.5 mg to 2 mg. Pharmacokinetic parameters for nalmefene after a 1 mg intravenous administration in adult male volunteers are listed in Table 1.

Table 1: Mean (CV%) Nalmefene Pharmacokinetic Parameters In Adult Males Following a 1 mg Intravenous Dose
Parameter | Young, N=18 | Elderly, N=11
Age | 19 to 32 | 62 to 80
Cp at 5 min. (ng/mL) | 3.7 (29) | 5.8 (38)
Vdss (L/kg) | 8.6 (19) | 8.6 (29)
Vc (L/kg) | 3.9 (29) | 2.8 (41)
AUC0-inf (ng-hr/mL) | 16.6 (27) | 17.3 (14)
Terminal T1/2 (hr) | 10.8 (48) | 9.4 (49)
Clplasma (L/hr/kg) | 0.8 (23) | 0.8 (18)

ABSORPTION

Nalmefene was completely bioavailable following intramuscular or subcutaneous administration in 12 male volunteers relative to intravenous nalmefene. The relative bioavailabilities of intramuscular and subcutaneous routes of administration were 101.5% ± 8.1% (Mean ± SD) and 99.7% ± 6.9%, respectively. Nalmefene will be administered primarily as an intravenous bolus, however, nalmefene can be given intra-muscularly (IM) or subcutaneously (SC) if venous access cannot be established. While the time to maximum plasma nalmefene concentration was 2.3 ± 1.1 hours following intramuscular and 1.5 ± 1.2 hours following subcutaneous administrations, therapeutic plasma concentrations are likely to be reached within 5 to 15 minutes after a 1 mg dose in an emergency. Because of the variability in the speed of absorption for IM & SC dosing, and the inability to titrate to effect, great care should be taken if repeated doses must be given by these routes.

DISTRIBUTION

Following a 1 mg parenteral dose, nalmefene was rapidly distributed. In a study of brain receptor occupancy, a 1 mg dose of nalmefene blocked over 80% of brain opioid receptors within 5 minutes after administration. The apparent volumes of distribution centrally (Vc) and at steady-state (Vdss) are 3.9 ± 1.1 L/kg and 8.6 ± 1.7 L/kg, respectively. Ultrafiltration studies of nalmefene have demonstrated that 45% (CV 4.1%) is bound to plasma proteins over a concentration range of 0.1 to 2 mcg/mL. An in vitro determination of the distribution of nalmefene in human blood demonstrated that nalmefene distributed 67% (CV 8.7%) into red blood cells and 39% (CV 6.4%) into plasma. The whole blood to plasma ratio was 1.3 (CV 6.6%) over the nominal concentration range in whole blood from 0.376 to 30 ng/mL.

METABOLISM

Nalmefene is metabolized by the liver, primarily by glucuronide conjugation, and excreted in the urine. Nalmefene is also metabolized to trace amounts of an N-dealkylated metabolite. Nalmefene glucuronide is inactive and the N-dealkylated metabolite has minimal pharmacological activity. Less than 5% of nalmefene is excreted in the urine unchanged. Seventeen percent (17%) of the nalmefene dose is excreted in the feces. The plasma concentration-time profile in some subjects suggests that nalmefene undergoes enterohepatic recycling.

ELIMINATION

After intravenous administration of 1 mg nalmefene hydrochloride injection to normal males (ages 19 to 32), plasma concentrations declined biexponentially with a redistribution and a terminal elimination half-life of 41 ± 34 minutes and 10.8 ± 5.2 hours, respectively. The systemic clearance of nalmefene is 0.8 ± 0.2 L/hr/kg and the renal clearance is 0.08 ± 0.04 L/hr/kg.

Special Populations

ELDERLY

Dose proportionality was observed in nalmefene AUC0-inf following 0.5 to 2 mg intravenous administration to elderly male subjects. Following a 1 mg intravenous nalmefene dose, there were no significant differences between young (19 to 32 years) and elderly (62 to 80 years) adult male subjects with respect to plasma clearance, steady-state volume of distribution, or half-life. There was an apparent age-related decrease in the central volume of distribution (young: 3.9 ± 1.1 L/kg, elderly: 2.8 ± 1.1 L/kg) that resulted in a greater initial nalmefene concentration in the elderly group. While initial nalmefene plasma concentrations were transiently higher in the elderly, it would not be anticipated that this population would require dosing adjustment. No clinical adverse events were noted in the elderly following the 1 mg intravenous nalmefene dose.

PATIENTS WITH HEPATIC IMPAIRMENT

Subjects with hepatic disease, when compared to matched normal controls, had a 28.3% decrease in plasma clearance of nalmefene (0.56 ± 0.21 L/hr/kg versus 0.78 ± 0.24 L/hr/kg, respectively). Elimination half-life increased from 10.2 ± 2.2 hours to 11.9 ± 2.0 hours in the hepatically impaired. No dosage adjustment is recommended since nalmefene will be administered as an acute course of therapy.

PATIENTS WITH RENAL IMPAIRMENT

There was a statistically significant 27% decrease in plasma clearance of nalmefene in the end-stage renal disease (ESRD) population during interdialysis (0.57 ± 0.20 L/hr/kg) and a 25% decreased plasma clearance in the ESRD population during intradialysis (0.59 ± 0.18 L/hr/kg) compared to normal patients (0.79 ± 0.24 L/hr/kg). The elimination half-life was prolonged in ESRD patients from 10.2 ± 2.2 hours in normal patients to 26.1 ± 9.9 hours (see DOSAGE AND ADMINISTRATION).

GENDER DIFFERENCES

There has not been sufficient pharmacokinetic study to make a definitive statement as to whether the pharmacokinetics of nalmefene differs between the genders.

CLINICAL TRIALS

Nalmefene hydrochloride injection has been administered to reverse the effects of opioids after general anesthesia and in the treatment of overdose. It has also been used to reverse the systemic effects of intrathecal opioids.

Reversal of Postoperative Opioid Depression

Nalmefene hydrochloride injection (N=326) was studied in 5 controlled trials in patients who had received morphine or fentanyl intraoperatively. The primary efficacy criterion was the reversal of respiratory depression. A positive reversal was defined as both an increase in respiratory rate by 5 breaths per minute and a minimum respiratory rate of 12 breaths per minute. Five minutes after administration, initial single nalmefene hydrochloride injection doses of 0.1, 0.25, 0.5, or 1 mcg/kg had effectively reversed respiratory depression in a dose-dependent manner. Twenty minutes after initial administration, respiratory depression had been effectively reversed in most patients receiving cumulative doses within the recommended range (0.1 to 1 mcg/kg). Total doses of nalmefene hydrochloride injection above 1 mcg/kg did not increase the therapeutic response. The postoperative administration of nalmefene hydrochloride at the recommended doses did not prevent the analgesic response to subsequently administered opioids.

Reversal of the Effect of Intrathecally Administered Opioids

Intravenous nalmefene hydrochloride at doses of 0.5 and 1 mcg/kg was administered to 47 patients given intrathecal morphine. One to 2 doses of 0.5 and 1 mcg/kg nalmefene hydrochloride reversed respiratory depression in most patients. The administration of nalmefene hydrochloride at the recommended doses did not prevent the analgesic response to subsequently administered opioids.

Management of Known or Suspected Opioid Overdose

Nalmefene hydrochloride injection (N=284) at doses of 0.5 mg to 2 mg was studied in 4 trials of patients who were presumed to have taken an opioid overdose. Nalmefene hydrochloride injection doses of 0.5 mg to 1 mg effectively reversed respiratory depression within 2 to 5 minutes in most patients subsequently confirmed to have opioid overdose. A total dose greater than 1.5 mg did not increase the therapeutic response.

INDICATIONS AND USAGE

Nalmefene hydrochloride injection is indicated for the complete or partial reversal of opioid drug effects, including respiratory depression, induced by either natural or synthetic opioids.

Nalmefene hydrochloride injection is indicated in the management of known or suspected opioid overdose.

CONTRAINDICATIONS

Nalmefene hydrochloride injection is contraindicated in patients with a known hypersensitivity to the product.

WARNINGS

Use of Nalmefene Hydrochloride Injection in Emergencies

Nalmefene hydrochloride injection, like all drugs in this class, is not the primary treatment for ventilatory failure. In most emergency settings, treatment with nalmefene hydrochloride injection should follow, not precede, the establishment of a patent airway, ventilatory assistance, administration of oxygen, and establishment of circulatory access.

Risk of Recurrent Respiratory Depression

Accidental overdose with long acting opioids [such as methadone and levo-alpha-acetylmethadol (LAAM)] may result in prolonged respiratory depression. Respiratory depression in both the postoperative and overdose setting may be complex and involve the effects of anesthetic agents, neuromuscular blockers, and other drugs. While nalmefene hydrochloride injection has a longer duration of action than naloxone in fully reversing doses, the physician should be aware that a recurrence of respiratory depression is possible, even after an apparently adequate initial response to nalmefene hydrochloride injection treatment.

Patients treated with nalmefene hydrochloride injection should be observed until, in the opinion of the physician, there is no reasonable risk of recurrent respiratory depression.

PRECAUTIONS

General

CARDIOVASCULAR RISKS WITH NARCOTIC ANTAGONISTS

Pulmonary edema, cardiovascular instability, hypotension, hypertension, ventricular tachycardia, and ventricular fibrillation have been reported in connection with opioid reversal in both postoperative and emergency department settings. In many cases, these effects appear to be the result of abrupt reversal of opioid effects.

Although nalmefene hydrochloride injection has been used safely in patients with pre-existing cardiac disease, all drugs of this class should be used with caution in patients at high cardiovascular risk or who have received potentially cardiotoxic drugs (see DOSAGE AND ADMINISTRATION).

RISK OF PRECIPITATED WITHDRAWAL

Nalmefene hydrochloride injection, like other opioid antagonists, is known to produce acute withdrawal symptoms and, therefore, should be used with extreme caution in patients with known physical dependence on opioids or following surgery involving high doses of opioids. Imprudent use or excessive doses of opioid antagonists in the postoperative setting has been associated with hypertension, tachycardia, and excessive mortality in patients at high risk for cardiovascular complications (see PRECAUTIONS).

INCOMPLETE REVERSAL OF BUPRENORPHINE

Preclinical studies have shown that nalmefene at doses up to 10 mg/kg (437 times the maximum recommended human dose) produced incomplete reversal of buprenorphine-induced analgesia in animal models. This appears to be a consequence of a high affinity and slow displacement of buprenorphine from the opioid receptors. Hence, nalmefene hydrochloride injection may not completely reverse buprenorphine-induced respiratory depression.

Drug Interactions

Nalmefene hydrochloride injection has been administered after benzodiazepines, inhalational anesthetics, muscle relaxants, and muscle relaxant antagonists administered in conjunction with general anesthesia. It also has been administered in outpatient settings, both in trials in conscious sedation and in the emergency management of overdose following a wide variety of agents. No deleterious interactions have been observed.

Preclinical studies have shown that both flumazenil and nalmefene can induce seizures in animals. The coadministration of both flumazenil and nalmefene produced fewer seizures than expected in a study in rodents, based on the expected effects of each drug alone. Based on these data, an adverse interaction from the coadministration of the two drugs is not expected, but physicians should remain aware of the potential risk of seizures from agents in these classes.

Carcinogenesis, Mutagenesis, Impairment of Fertility

Nalmefene did not have mutagenic activity in the Ames test with five bacterial strains or the mouse lymphoma assay. Clastogenic activity was not observed in the mouse micronucleus test or in the cytogenic bone marrow assay in rats. However, nalmefene did exhibit a weak but significant clastogenic activity in the human lymphocyte metaphase assay in the absence but not in the presence of exogenous metabolic activation. Oral administration of nalmefene up to 1200 mg/m^2/day did not affect fertility, reproductive performance, and offspring survival in rats.

Use in Pregnancy

Reproduction studies have been performed in rats (up to 1200 mg/m^2/day) and rabbits (up to 2400 mg/m^2/day) by oral administration of nalmefene and in rabbits by intravenous administration up to 96 mg/m^2/day (114 times the human dose). There was no evidence of impaired fertility or harm to the fetus. There are, however, no adequate and well-controlled studies in pregnant women. Because animal reproduction studies are not always predictive of human response, this drug should be used during pregnancy only if clearly needed.

Nursing Mothers

Nalmefene and its metabolites were secreted into rat milk, reaching concentrations approximately three times those in plasma at one hour and decreasing to about half the corresponding plasma concentrations by 24 hours following bolus administration. As no clinical information is available, caution should be exercised when nalmefene hydrochloride injection is administered to a nursing woman.

Use in Pediatric Patients

Safety and effectiveness of nalmefene hydrochloride injection in pediatric patients have not been established.

Use in Neonates

The safety and effectiveness of nalmefene hydrochloride injection in neonates have not been established in clinical studies. In a preclinical study, nalmefene was administered by subcutaneous injection to rat pups at doses up to 205 mg/m^2/day throughout maternal lactation without producing adverse effects. A preclinical study evaluating the irritancy of the dosage form following arterial and venous administration in animals showed no vascular irritancy.

Nalmefene hydrochloride injection should only be used in the resuscitation of the newborn when, in the opinion of the treating physician, the expected benefits outweigh the risks.

Geriatric Use

Clinical studies of nalmefene hydrochloride injection did not include sufficient number of subjects aged 65 and over to determine whether they respond differently from younger subjects. Other reported clinical experience has not identified differences in responses between the elderly and younger patients. In general, dose selection for an elderly patient should be cautious, usually starting at the low end of the dosing range, reflecting the greater frequency of decreased hepatic, renal, or cardiac function, and of concomitant disease or other drug therapy.

ADVERSE REACTIONS

Adverse event information was obtained following administration of nalmefene hydrochloride injection to 152 normal volunteers and in controlled clinical trials to 1127 patients for the treatment of opioid overdose or for postoperative opioid reversal.

Nalmefene was well tolerated and showed no serious toxicity during experimental administration to healthy individuals, even when given at 15 times the highest recommended dose. In a small number of subjects, at doses exceeding the recommended nalmefene hydrochloride injection dose, nalmefene produced symptoms suggestive of reversal of endogenous opioids, such as have been reported for other narcotic antagonist drugs. These symptoms (nausea, chills, myalgia, dysphoria, abdominal cramps, and joint pain) were usually transient and occurred at very low frequency.

Such symptoms of precipitated opioid withdrawal at the recommended clinical doses were seen in both postoperative and overdose patients who were later found to have had histories of covert opioid use. Symptoms of precipitated withdrawal were similar to those seen with other opioid antagonists, were transient following the lower doses used in the postoperative setting, and more prolonged following the administration of the larger doses used in the treatment of overdose.

Tachycardia and nausea following the use of nalmefene in the postoperative setting were reported at the same frequencies as for naloxone at equivalent doses. The risk of both these adverse events was low at doses giving partial opioid reversal and increased with increases in dose. Thus, total doses larger than 1 mcg/kg in the postoperative setting and 1.5 mg/70 kg in the treatment of overdose are not recommended.

Relative Frequencies of Common Adverse Reactions with an Incidence Greater than 1% (all patients, all clinical settings)
Adverse Event | Nalmefene N=1127 | Naloxone N=369 | Placebo N=77
Nausea | 18% | 18% | 6%
Vomiting | 9% | 7% | 4%
Tachycardia | 5% | 8% | -
Hypertension | 5% | 7% | -
Postoperative pain | 4% | 4% | N/A
Fever | 3% | 4% | -
Dizziness | 3% | 4% | 1%
Headache | 1% | 1% | 4%
Chills | 1% | 1% | -
Hypotension | 1% | 1% | -
Vasodilation | 1% | 1% | -

Incidence less than 1%

CARDIOVASCULAR: Bradycardia, arrhythmia

DIGESTIVE: Diarrhea, dry mouth

NERVOUS SYSTEM: Somnolence, depression, agitation, nervousness, tremor, confusion, withdrawal syndrome, myoclonus

RESPIRATORY: Pharyngitis

SKIN: Pruritus

UROGENITAL: Urinary retention

The incidence of adverse events was highest in patients who received more than the recommended dose of nalmefene hydrochloride injection.

Laboratory findings

Transient increases in CPK were reported as adverse events in 0.5% of the postoperative patients studied. These increases were believed to be related to surgery and not believed to be related to the administration of nalmefene hydrochloride injection. Increases in AST were reported as adverse events in 0.3% of the patients receiving either nalmefene or naloxone. The clinical significance of this finding is unknown. No cases of hepatitis or hepatic injury due to either nalmefene or naloxone were observed in the clinical trials.

DRUG ABUSE AND DEPENDENCE

Nalmefene hydrochloride injection is an opioid antagonist with no agonist activity. It has no demonstrated abuse potential, is not addictive, and is not a controlled substance.

OVERDOSAGE

Intravenous doses of up to 24 mg of nalmefene, administered to healthy volunteers in the absence of opioid agonists, produced no serious adverse reactions, severe signs or symptoms, or clinically significant laboratory abnormalities. As with all opioid antagonists, use in patients physically dependent on opioids can result in precipitated withdrawal reactions that may result in symptoms that require medical attention. Treatment of such cases should be symptomatic and supportive. Administration of large amounts of opioids to patients receiving opioid antagonists in an attempt to overcome a full blockade has resulted in adverse respiratory and circulatory reactions.

DOSAGE AND ADMINISTRATION

Important Information - Dosage Form

Nalmefene hydrochloride injection is supplied in a 2 mL vial as a 1 mg/mL concentration suitable for the management of overdose. Proper steps should be taken to prevent use of the incorrect concentration.

General Principles

Nalmefene hydrochloride injection should be titrated to reverse the undesired effects of opioids. Once adequate reversal has been established, additional administration is not required and may actually be harmful due to unwanted reversal of analgesia or precipitated withdrawal.

Duration of Action

The duration of action of nalmefene hydrochloride injection is as long as most opioid analgesics. The apparent duration of action of nalmefene hydrochloride injection will vary, however, depending on the half-life and plasma concentration of the narcotic being reversed, the presence or absence of other drugs affecting the brain or muscles of respiration, and the dose of nalmefene hydrochloride injection administered. Partially reversing doses of nalmefene hydrochloride injection (1 mcg/kg) lose their effect as the drug is redistributed through the body, and the effects of these low doses may not last more than 30 to 60 minutes in the presence of persistent opioid effects. Fully reversing doses (1 mg/70 kg) have been shown to last many hours in both experimental and clinical studies, but may complicate the management of patients who are in pain, at high cardiovascular risk, or who are physically dependent on opioids.

The recommended doses represent a compromise between a desirable controlled reversal and the need for prompt response and adequate duration of action. Using higher dosages or shorter intervals between incremental doses is likely to increase the incidence and severity of symptoms related to acute withdrawal such as nausea, vomiting, elevated blood pressure, and anxiety.

Patients Tolerant to or Physically Dependent on Opioids

Nalmefene hydrochloride injection may cause acute withdrawal symptoms in individuals who have some degree of tolerance to and dependence on opioids. These patients should be closely observed for symptoms of withdrawal following administration of the initial and subsequent injections of nalmefene hydrochloride injection. Subsequent doses should be administered with intervals of at least 2 to 5 minutes between doses to allow the full effect of each incremental dose of nalmefene hydrochloride injection to be reached.

Management of Known or Suspected Opioid Overdose

The recommended initial dose of nalmefene hydrochloride injection for non-opioid dependent patients is 0.5 mg/70 kg. If needed, this may be followed by a second dose of 1 mg/70 kg, 2 to 5 minutes later. If a total dose of 1.5 mg/70 kg has been administered without clinical response, additional nalmefene hydrochloride injection is unlikely to have an effect. Patients should not be given more nalmefene hydrochloride injection than is required to restore the respiratory rate to normal, thus minimizing the likelihood of cardiovascular stress and precipitated withdrawal syndrome.

If there is a reasonable suspicion of opioid dependency, a challenge dose of nalmefene hydrochloride injection 0.1 mg/70 kg should be administered initially. If there is no evidence of withdrawal in 2 minutes, the recommended dosing should be followed.

Nalmefene hydrochloride injection had no effect in cases where opioids were not responsible for sedation and hypoventilation. Therefore, patients should only be treated with nalmefene hydrochloride injection when the likelihood of an opioid overdose is high, based on a history of opioid overdose or the clinical presentation of respiratory depression with concurrent pupillary constriction.

Repeated Dosing

Nalmefene hydrochloride injection is the longest acting of the currently available parenteral opioid antagonists. If recurrence of respiratory depression does occur, the dose should again be titrated to clinical effect using incremental doses to avoid over-reversal.

Hepatic and Renal Disease

Hepatic disease and renal failure substantially reduce the clearance of nalmefene (see Pharmacokinetics). For single episodes of opioid antagonism, adjustment of nalmefene hydrochloride injection dosage is not required. However, in patients with renal failure, the incremental doses should be delivered slowly (over 60 seconds) to minimize the hypertension and dizziness reported following the abrupt administration of nalmefene to such patients.

Loss of Intravenous Access

Should intravenous access be lost or not readily obtainable, a pharmacokinetic study has shown that a single dose of nalmefene hydrochloride injection should be effective within 5 to 15 minutes after intramuscular or subcutaneous doses of 1 mg (see Pharmacokinetics).

SAFETY AND HANDLING

Nalmefene hydrochloride injection is distributed in sealed vials which represent no known risk to health care workers. As with all parenterals, care should be taken to prevent the generation and inhalation of aerosols during preparation and use. Dermal absorption of spilled nalmefene hydrochloride injection should be prevented by prompt removal of contaminated clothing and rinsing the skin thoroughly with cool water.

Parenteral drug products should be inspected visually for particulate matter and discoloration prior to administration, whenever solution and container permit.

HOW SUPPLIED

Nalmefene hydrochloride injection is available in the following presentation:

A single-dose vial containing 2 mg/2 mL (1 mg/mL) of nalmefene base.

Box of 10 | NDC 59011-960-10

STORAGE AND HANDLING

Store at 20° to 25°C (68° to 77°F) [see USP Controlled Room Temperature].

Store in original carton.

Protect from light.

Discard unused portion.

For additional information, contact Purdue Pharma's Medical Information Department @ 1-888-726-7535.

Distributed by:
Purdue Pharma L.P.
Stamford, CT 06901-3431

Manufactured by:
PCI San Diego, Inc.
San Diego, CA 92121

306077-0B

Revised: 08/2025

PRINCIPAL DISPLAY PANEL - 2 mL Vial Carton

NDC 59011-960-10
10 x 2 mL Single-Dose Vials

Nalmefene Hydrochloride Injection

2 mg/2 mL (1 mg/mL)
(nalmefene base)

Rx Only

Each mL contains: Nalmefene hydrochloride
(equivalent to 1 mg nalmefene base), Sodium Chloride,
USP, Hydrochloric Acid, NF, and Water for Injection, USP
This unit package is not to be broken for resale.
Discard unused portion.

See package insert for dosage and directions for use.
Storage: Store at 20° to 25°C (68° to 77°F)
[see USP Controlled Room Temperature].
Store in original carton. Protect from light.